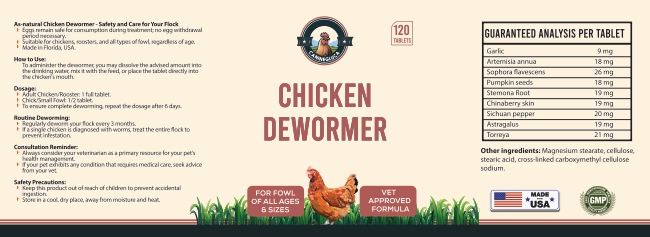 DRUG LABEL: Chicken Dewormer
NDC: 86202-0241 | Form: TABLET
Manufacturer: AMBIENCE FAMILY INC
Category: animal | Type: OTC ANIMAL DRUG LABEL
Date: 20240501

ACTIVE INGREDIENTS: GARLIC 9 mg/1 g; ARTEMISIA ANNUA POLLEN 18 mg/1 g; SOPHORA FLAVESCENS ROOT 18 mg/1 g; PUMPKIN SEED 18 mg/1 g; STEMONA JAPONICA ROOT 18 mg/1 g; ASTRAGALUS CHINENSIS SEED 18 mg/1 g; TORREYA NUCIFERA SEED OIL 18 mg/1 g

Chicken Dewormer

WARNINGS AND PRECAUTIONS

Not for use in humans. Keep out of reach of children. Protective gloves should be used and care should be taken when handling the product to avoid skin and eye exposure and accidental ingestion. Accidental exposure may result in skin and eye irritation. Accidental ingestion may cause gastrointestinal disturbances and hypersensitivity reactions in humans.

WARNINGS AND PRECAUTIONS

Not for use in humans. Keep out of reach of children. Protective gloves should be used and care should be taken when handling the product to avoid skin and eye exposure and accidental ingestion. Accidental exposure may result in skin and eye irritation. Accidental ingestion may cause gastrointestinal disturbances and hypersensitivity reactions in humans.

PACKAGE LABEL

Content of Labling